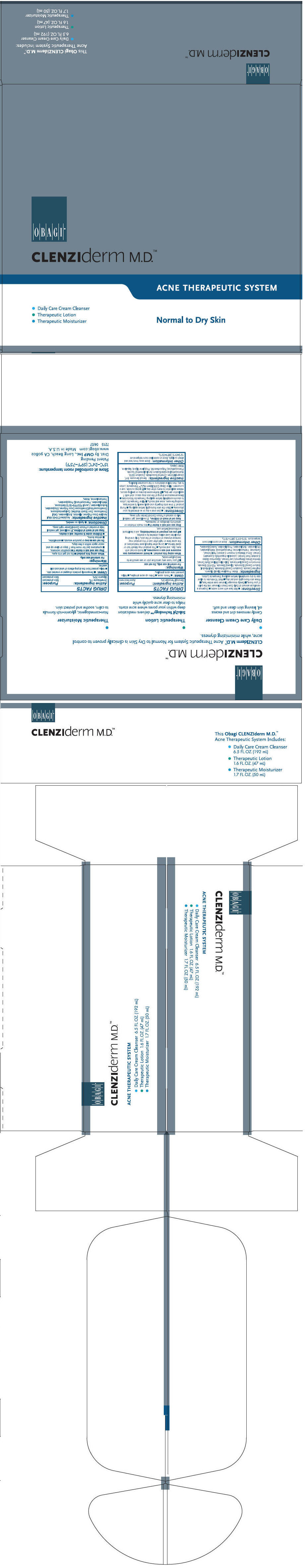 DRUG LABEL: CLENZIDERM NORMAL TO DRY SKIN
NDC: 62032-512 | Form: KIT | Route: TOPICAL
Manufacturer: OMP, INC.
Category: otc | Type: HUMAN OTC DRUG LABEL
Date: 20171219

ACTIVE INGREDIENTS: GLYCERIN 200 mg/1 mL; BENZOYL PEROXIDE 50 mg/1 mL
INACTIVE INGREDIENTS: ALLANTOIN; CARBOMER INTERPOLYMER TYPE A (ALLYL SUCROSE CROSSLINKED); CYCLOMETHICONE 5; LAURYL PEG/PPG-18/18 METHICONE; DIMETHICONE; TROLAMINE; WATER; PHENOXYETHANOL; ETHYLPARABEN; ISOBUTYLPARABEN; BUTYLPARABEN; PROPYLPARABEN; METHYLPARABEN; BENZYL BENZOATE; DICAPRYLYL ETHER; PROPYLENE GLYCOL; SQUALANE; POLYSORBATE 60; DIMETHYL ISOSORBIDE; PHENOXYETHANOL; EDETATE DISODIUM; BUTYLATED HYDROXYTOLUENE; WATER

CLENZIDERM NORMAL TO DRY SKIN
ACNE THERAPEUTIC SYSTEM

Directions

- Wet face with warm water.
- Dispense a nickel size amount of Daily Care Cream Cleanser into the palm of your hand.
- Gently massage Cleanser over entire face.
- Rinse skin thoroughly and pat dry.
- Wait 10 minutes to allow skin to dry completely before applying Therapeutic Lotion.

Ingredients

Water, Propylene Glycol, Glycerin, Arginine Cocoate, Disodium Cocoyl Glutamate, Cetyl Alcohol, Sodium Cocoyl Glutamate, Glyceryl Stearate, PEG-100 Stearate, Ammonium Cocoyl Isethionate, Salix Alba (Willow) Bark Extract, Mentha Citrata (Bergamot) Leaf Extract, Glycyrrhiza Glabra (Licorice) Root Extract, Lavandula Angustifolia (Lavender) Extract, Citrus Medica Limonum (Lemon) Peel Extract, Carbomer, Triethanolamine, Phenoxyethanol, Methylparaben, Ethylparaben, Butylparaben, Propylparaben, Isobutylparaben.

Other Information

Store at controlled room temperature: 15°C–24°C (59°F–75°F).

Therapeutic Lotion

DRUG FACTS

Active Ingredient

Benzoyl Peroxide 5%

Purpose

Acne treatment

Uses

- Treats acne.
- Dries up acne pimples.
- Helps prevent new acne pimples.

Warnings

For external use only. Do not use

- If you have very sensitive skin or are sensitive to benzoyl peroxide.

When using this product

- Avoid unneccessary sun exposure and use a sunscreen.
- Avoid contact with eyes, lips, and mouth.
- This product may bleach hair or dyed fabrics.
- Using other topical acne medications at the same time or right after use of this product may increase dryness or irritation of the skin. Only one drug should be used unless directed by a doctor.
- If you are pregnant or breast-feeding, ask a healthcare professional before use.

Stop use and ask a doctor if

- too much irritation or sensitivity develops or increases.

Keep out of reach of children. If swallowed, get medical help or contact a Poison Control Center right away.

Directions

- Use once a day or as directed by your physician.
- Clean the skin thoroughly before applying.
- Pump product 1 time onto fingertip and apply evenly to entire face, avoiding the eyes, nose and mouth.
- Allow Therapeutic Lotion to absorb completely before applying Therapeutic Moisturizer.
- Because excessive drying of the skin may occur, start with 1 application per day.
- If bothersome dryness or peeling occurs, reduce application to every other day.
- If going outside, use a sunscreen: Allow Obagi CLENZIderm M.D.™ Therapeutic Lotion to dry, then follow directions in the sunscreen labeling.

Inactive Ingredients

Benzyl Benzoate, BHT, Dicaprylyl Ether, Dimethyl Isosorbide, Disodium EDTA, Hydroxyethyl Acrylate/Sodium Acryloyldimethyl Taurate, Phenoxyethanol, Polysorbate 60, Propylene Glycol, Squalane, Water (aqua).

Other Information

Store away from heat and direct sunlight. Store at controlled room temperature: 15°C–24°C (59°F–75°F).

Therapeutic Moisturizer

DRUG FACTS

ACTIVE INGREDIENT

Active Ingredients: | Purpose:
Dimethicone 1% | Skin protectant
Glycerin 20% | Skin protectant

Uses

- Temporarily protects chapped or cracked skin.
- Helps protect from the drying effects of wind and cold weather.

Warnings

For external use only.

When using this product

- Do not get into eyes.

Stop use and ask a doctor if

- condition worsens.
- symptoms last for more than 7 days or clear up and occur again within a few days.

Do not use

- deep or puncture wounds.
- animal bites.
- serious burns.

- Children under 6 months: ask a doctor.

Keep out of reach of children. If swallowed, get medical help or contact a Poison Control Center right away.

Directions

- Apply as needed.

Inactive Ingredients

Acrylates/C10-30 Alkyl Acrylate Cross Polymer, Allantoin, Butylparaben, Cetyl Dimethicone, Corn Starch Modified, Cyclopentasiloxane, Dimethicone/Vinyl Dimethicone Cross Polymer, Ethylparaben, Isobutylparaben, Lauryl PEG/PPG-18/18 Methicone, Metyhlparaben, Phenoxyethanol, Propylparaben, Triethanolamine, Water.

Dist. By OMP Inc., Long Beach, CA 90802

PRINCIPAL DISPLAY PANEL - Kit Carton

OBAGI®

CLENZIderm M.D.™

ACNE THERAPEUTIC SYSTEM

- Daily Care Cream Cleanser
- Therapeutic Lotion
- Therapeutic Moisturizer

Normal to Dry Skin